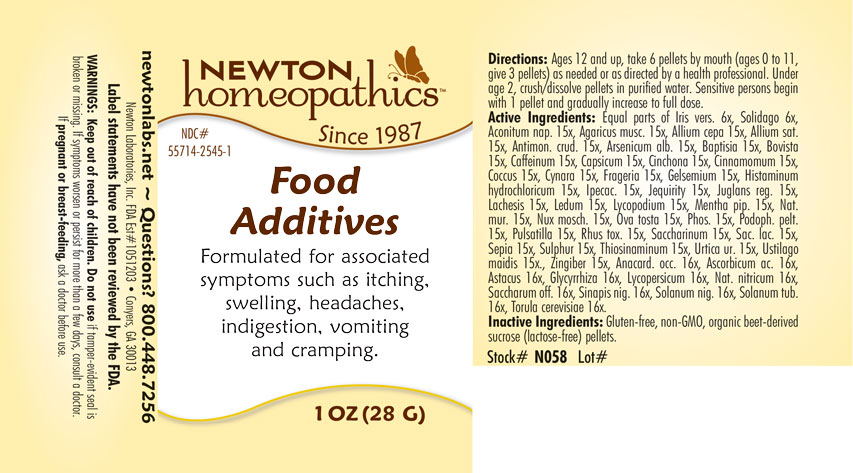 DRUG LABEL: Food Additives
NDC: 55714-2545 | Form: PELLET
Manufacturer: Newton Laboratories, Inc.
Category: homeopathic | Type: HUMAN OTC DRUG LABEL
Date: 20201130

ACTIVE INGREDIENTS: ARSENIC TRIOXIDE 15 [hp_X]/1 g; BAPTISIA TINCTORIA ROOT 15 [hp_X]/1 g; LYCOPERDON UTRIFORME FRUITING BODY 15 [hp_X]/1 g; CAFFEINE 15 [hp_X]/1 g; CAPSICUM 15 [hp_X]/1 g; CINCHONA OFFICINALIS BARK 15 [hp_X]/1 g; CINNAMON 15 [hp_X]/1 g; PROTORTONIA CACTI 15 [hp_X]/1 g; CYNARA SCOLYMUS LEAF 15 [hp_X]/1 g; ALPINE STRAWBERRY 15 [hp_X]/1 g; GELSEMIUM SEMPERVIRENS ROOT 15 [hp_X]/1 g; HISTAMINE DIHYDROCHLORIDE 15 [hp_X]/1 g; SOLIDAGO VIRGAUREA FLOWERING TOP 6 [hp_X]/1 g; URTICA URENS 15 [hp_X]/1 g; GINGER 15 [hp_X]/1 g; MENTHA PIPERITA 15 [hp_X]/1 g; ABRUS PRECATORIUS SEED 15 [hp_X]/1 g; JUGLANS REGIA LEAF 15 [hp_X]/1 g; USTILAGO MAYDIS 15 [hp_X]/1 g; LACHESIS MUTA VENOM 15 [hp_X]/1 g; NUTMEG 15 [hp_X]/1 g; PODOPHYLLUM 15 [hp_X]/1 g; SULFUR 15 [hp_X]/1 g; ASTACUS ASTACUS 16 [hp_X]/1 g; GLYCYRRHIZA GLABRA 16 [hp_X]/1 g; SOLANUM TUBEROSUM 16 [hp_X]/1 g; SACCHAROMYCES CEREVISIAE 16 [hp_X]/1 g; LACTOSE, UNSPECIFIED FORM 15 [hp_X]/1 g; SEPIA OFFICINALIS JUICE 15 [hp_X]/1 g; SUCROSE 16 [hp_X]/1 g; EGG SHELL, COOKED 15 [hp_X]/1 g; LYCOPODIUM CLAVATUM SPORE 15 [hp_X]/1 g; RHODODENDRON TOMENTOSUM LEAFY TWIG 15 [hp_X]/1 g; ASCORBIC ACID 16 [hp_X]/1 g; BLACK MUSTARD SEED 16 [hp_X]/1 g; SOLANUM NIGRUM WHOLE 16 [hp_X]/1 g; ANACARDIUM OCCIDENTALE FRUIT 16 [hp_X]/1 g; SOLANUM LYCOPERSICUM 16 [hp_X]/1 g; SODIUM NITRITE 16 [hp_X]/1 g; SODIUM CHLORIDE 15 [hp_X]/1 g; ANEMONE PULSATILLA 15 [hp_X]/1 g; TOXICODENDRON PUBESCENS LEAF 15 [hp_X]/1 g; ALLYLTHIOUREA 15 [hp_X]/1 g; IRIS VERSICOLOR ROOT 6 [hp_X]/1 g; IPECAC 15 [hp_X]/1 g; ACONITUM NAPELLUS 15 [hp_X]/1 g; AMANITA MUSCARIA FRUITING BODY 15 [hp_X]/1 g; ONION 15 [hp_X]/1 g; GARLIC 15 [hp_X]/1 g; PHOSPHORUS 15 [hp_X]/1 g; SACCHARIN 15 [hp_X]/1 g; ANTIMONY TRISULFIDE 15 [hp_X]/1 g
INACTIVE INGREDIENTS: SUCROSE CARAMEL

Food 2545P

INDICATIONS & USAGE SECTION

Formulated for associated symptoms such as itching, swelling, headaches, indigestiion, vomiting and cramping.

DOSAGE & ADMINISTRATION SECTION

Directions: Ages 12 and up, take 6 pellets by mouth (ages 0 to 11, give 3 pellets) as needed or directed by a health professional. Under age 2, crush/dissolve pellets in purified water. Sensitive persons begin with 1 pellet and gradually increase to full dose.

OTC - ACTIVE INGREDIENT SECTION

Equal parts of Iris versicolor 6x, Solidago virgaurea 6x, Aconitum napellus 15x, Agaricus muscarius 15x, Allium cepa 15x, Allium sativum 15x, Antimonium crudum 15x, Arsenicum album 15x, Baptisia tinctoria 15x, Bovista 15x, Caffeinum 15x, Capsicum annuum 15x, Cinchona officinalis 15x, Cinnamomum 15x, Coccus cacti 15x, Cynara scolymus 15x, Fragaria vesca 15x, Gelsemium sempervirens 15x, Histaminum hydrochloricum 15x, Ipecacuanha 15x, Jequerity 15x, Juglans regia 15x, Lachesis mutus 15x, Ledum palustre 15x, Lycopodium clavatum 15x, Mentha piperita 15x, Natrum muriaticum 15x, Nux moschata 15x, Ova tosta 15x, Phosphorus 15x, Podophyllum peltatum 15x, Pulsatilla 15x, Rhus toxicodendron 15x, Saccharinum 15x, Saccharum lactis 15x, Sepia 15x, Sulphur 15x, Thiosinaminum 15x, Urtica urens 15x, Ustilago maidis 15x, Zingiber officinale 15x, Anacardium occidentale 16x, Ascorbicum acidum 16x, Astacus fluviatilis 16x, Glycyrrhiza glabra 16x, Lycopersicum esculentum 16x, Natrum nitricum 16x, Saccharum officinale 16x, Sinapis nigra 16x, Solanum nigrum 16x, Solanum tuberosum 16x, Torula cerevisiae 16x.

OTC - PURPOSE SECTION

Formulated for associated symtoms such as itching, swelling, headaches, indigestion, vomiting and cramping.

INACTIVE INGREDIENT SECTION

Inactive Ingredients: Gluten-free, non-GMO, organic beet-derived sucrose (lactose-free) pellets.

QUESTIONS SECTION

newtonlabs.net - Questions? 800.448.7256

Newton Laboratories, Inc. FDA Est # 1051203 Conyers, GA 30013

WARNINGS SECTION

WARNINGS: Keep out of reach of children. Do not use if tamper-evident seal is broken or missing. If symptoms worsen or persist for more than a few days, consult a doctor. If pregnant or breast-feeding, ask a doctor before use.

OTC - PREGNANCY OR BREAST FEEDING SECTION

If pregnant or breast-feeding, ask a doctor before use.

OTC - KEEP OUT OF REACH OF CHILDREN SECTION

Keep out of reach of children.